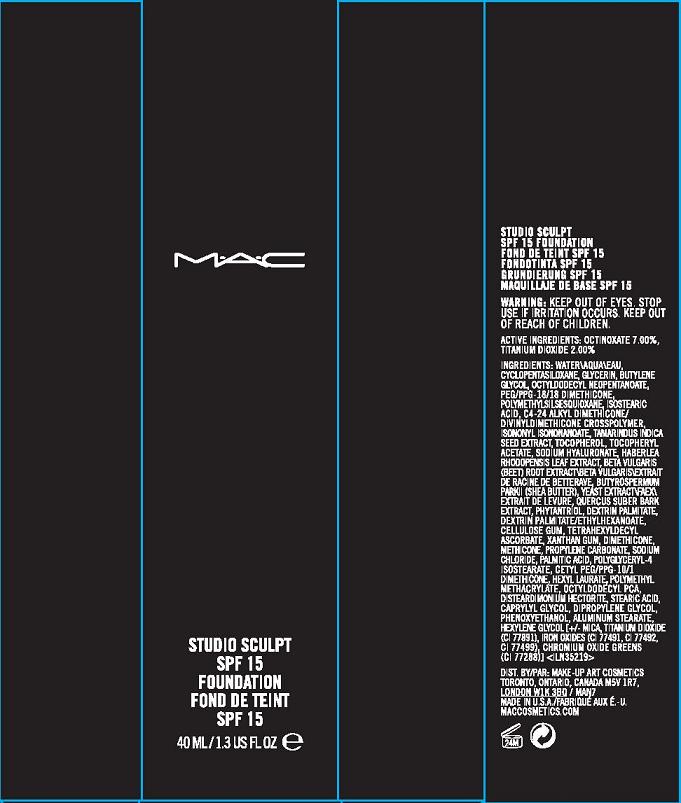 DRUG LABEL: STUDIO SCULPT
NDC: 40046-0032 | Form: LIQUID
Manufacturer: MAKE UP ART COSMETICS
Category: otc | Type: HUMAN OTC DRUG LABEL
Date: 20100228

ACTIVE INGREDIENTS: OCTINOXATE 7.0 mL/100 mL; TITANIUM DIOXIDE 2.0 mL/100 mL
INACTIVE INGREDIENTS: GLYCERIN; CYCLOMETHICONE 5; WATER; BUTYLENE GLYCOL; ISOSTEARIC ACID; TAMARINDUS INDICA SEED; .ALPHA.-TOCOPHEROL ACETATE, DL-; ALPHA-TOCOPHEROL, DL-; HYALURONATE SODIUM; SHEA BUTTER; PHENOXYETHANOL; FERRIC OXIDE RED; FERRIC OXIDE YELLOW

ACTIVE INGREDIENT

ACTIVE INGREDIENTS: OCTINOXATE 7.00% [] TITANIUM DIOXIDE 2.00%

INACTIVE INGREDIENT

INACTIVE INGREDIENTS: WATER [] CYCLOPENTASILOXANE [] GLYCERIN [] BUTYLENE GLYCOL [] OCTYLDODECYL NEOPENTANOATE [] PEG/PPG-18/18 DIMETHICONE [] POLYMETHYLSILSESQUIOXANE [] ISOSTEARIC ACID [] C4-24 ALKYL DIMETHICONE/DIVINYLDIMETHICONE CROSSPOLYMER [] ISONONYL ISONONANOATE [] TAMARINDUS INDICA SEED EXTRACT [] TOCOPHEROL [] TOCOPHERYL ACETATE [] SODIUM HYALURONATE [] HABERLEA RHODOPENSIS LEAF EXTRACT [] BUTYROSPERMUM PARKII (SHEA BUTTER) [] YEAST EXTRACT\FAEX\EXTRAIT DE LEVURE [] QUERCUS SUBER BARK EXTRACT [] PHYTANTRIOL [] DEXTRIN PALMITATE [] DEXTRIN PALMITATE/ETHYLHEXANOATE [] CELLULOSE GUM [] TETRAHEXYLDECYL ASCORBATE [] XANTHAN GUM [] DIMETHICONE [] METHICONE [] PROPYLENE CARBONATE [] SODIUM CHLORIDE [] PALMITIC ACID [] POLYGLYCERYL-4 ISOSTEARATE [] CETYL PEG/PPG-10/1 DIMETHICONE [] HEXYL LAURATE [] POLYMETHYL METHACRYLATE [] OCTYLDODECYL PCA [] DISTEARDIMONIUM HECTORITE [] STEARIC ACID [] CAPRYLYL GLYCOL [] DIPROPYLENE GLYCOL [] PHENOXYETHANOL [] ALUMINUM STEARATE [] HEXYLENE GLYCOL [] [+/- MICA [] TITANIUM DIOXIDE (CI 77891) [] IRON OXIDES (CI 77491, CI 77492, CI 77499) [] CHROMIUM OXIDE GREENS (CI 77288)]

WARNINGS

WARNING: KEEP OUR OF EYES. STOP USE IF IRRITATION OCCURS.

KEEP OUT OF REACH OF CHILDREN.

PACKAGE LABEL

PRINCIPAL DISPLAY PANEL:

MAC

STUDIO SCULPT

SPF 15 FOUNDATION

40 ML/ 1.3 US FL OZ

DISTR BY MAKE-UP ART COSMETICS

TORONTO, ONTARIO

CANADA